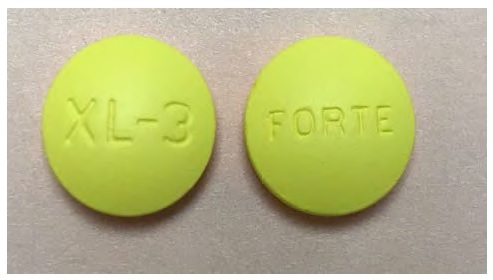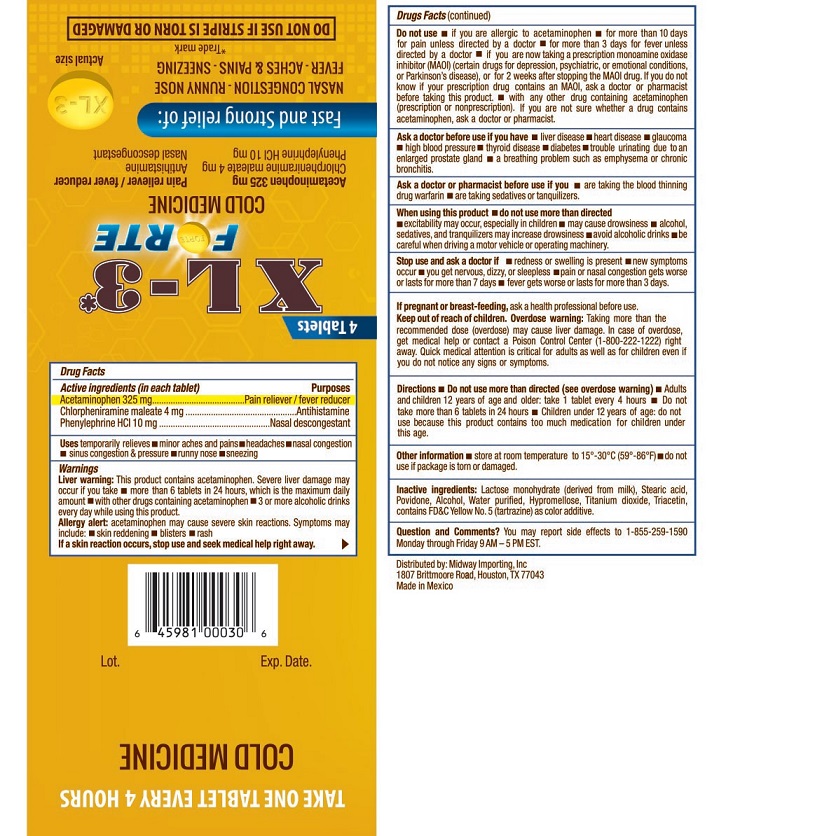 DRUG LABEL: Cold Medicine
NDC: 63654-601 | Form: TABLET
Manufacturer: Selder, S.A. de C.V.
Category: otc | Type: HUMAN OTC DRUG LABEL
Date: 20241024

ACTIVE INGREDIENTS: ACETAMINOPHEN 325 mg/1 1; CHLORPHENIRAMINE MALEATE 4 mg/1 1; PHENYLEPHRINE HYDROCHLORIDE 10 mg/1 1
INACTIVE INGREDIENTS: LACTOSE MONOHYDRATE; STEARIC ACID; POVIDONE; HYPROMELLOSES; TITANIUM DIOXIDE; FD&C YELLOW NO. 5; WATER; ALCOHOL; TRIACETIN

XL3FrteactmnphnchlrphnirmnphnylphrinhclSldr

Active ingredients (in each tablet)

Acetaminophen 325 mg
Chlorpheniramine maleate 4 mg
Phenylepherine HCl 10 mg

Purposes

Pain reliever/fever reducer
Antihistamine
Nasal decongestant

Uses

temporarily relieves ■ minor aches and pains ■ headaches ■ nasal congestion ■ sinus congestion & pressure ■ runny nose ■sneezing

Warnings

Liver warning: This product contains acetaminophen. Severe liver damage may occur if you take ■ more than 6 tablets in 24 hours, which is the maximum daily amount ■ with other drugs containing acetaminophen ■ 3 or more alcoholic drinks every day while using this product

Alergy alert acetaminophen may cause severe skin reactions. Symptoms may include ■ skin reddening ■ blisters ■ rash

If a skin reaction occurs, stop use and seek medical help right away

Do not use

■ If you are allergic to acetaminophen ■ more than 10 days unless directed by a doctor ■ for more than 3 days for fever unless directed by a doctor ■ if you are taking a monoamine oxidase inhibitor (MAOI) (certain drugs for depression, psychiatric, or emotional conditions, or Parkinson"s disease) or for 2 weeks after stopping the MAOI drug. If you do not know if your prescription drug contasins an MAOI, ask a doctor or pharmacist before taking this product. ■ with any other drug containing acetaminophen (prescription or nonprescription). If you are not sure whether a drug contains acetaminophen, ask a doctor or pharmacist.

Ask adoctor before use if you have

■ liver disease ■ heart disease ■ glaucoma ■ high blood pressure ■ thyroid disease ■ diabetes ■ trouble urinating due to enlarged prostate gland ■ a breathing problem such as emphysema or chronic bronchitis

Ask a doctor or pharmacist before use if you

■ are taking the blood thinning drug warfarin ■ are taking sedatives or tranquilizers

When using this product

■ do not use more than directed ■ excitability may occur, especially in children ■ may cause drowsiness ■ alcohol, sedatives and tranquilizers may increase drowsiness ■ avoid alcoholic drinks ■ be careful when driving a motor vehicle or operating machinery

Stop use and ask a doctor if

■ redness or swelling is present ■ new symptoms occur ■ you get nervous, dizzy, or sleepless ■ pain or nasal congestion gets worse or lasts for more than 7 days ■ fever gets worse or lasts for more than 3 days

Keep out of reach of children

If pregnant or breast-feeding, ask a health professional before use. Keep out of reach of children. Overdose warning: Taking more than the recommended dose (overdose) may cause liver damage. In case of overdose, get medical help or contact a Poison Control Center (1-800-222-1222) right away.Quick medical attention is critical for adults as well as for children even if you do not notice any signs or symptoms.

Directions

■ Do not use more than directed (see overdose warning) ■ Adults and children 12 years of age and older: take 1 tablet every 4 hours Do not take more than 6 tablets in 24 hours ■ Children under 12 years of age: do not use because this product contains to much medication for children under this age.

Other Information

■ store at room temperature 59-86F (15-30C) ■ do not use if package is torn or damaged

Inactive Ingredients

Lactose monohydrate (derived from milk), Stearic acid, Povidone, Alcohol, Water purified, Hypromellose, Titanium dioxide, Triacetin, contains FDC Yellow No. 5 (tartrazine) as color additive

Questions and Comments?

You may report side effects to 1-855-259-1590 Monday through Friday 9AM-5PM EST